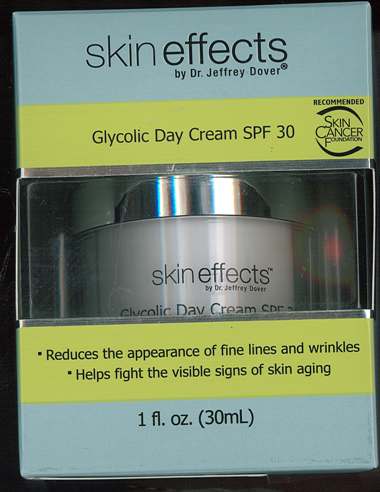 DRUG LABEL: Glycolic Day Cream SPF 30
NDC: 68634-0032 | Form: CREAM
Manufacturer: AMCOL Health and Beauty Solutions, Inc.
Category: otc | Type: HUMAN OTC DRUG LABEL
Date: 20100204

ACTIVE INGREDIENTS: Homosalate 0.1 mL/1 mL; Octisalate 0.05 mL/1 mL; Octocrylene 0.02 mL/1 mL; Oxybenzone 0.05 mL/1 mL; Avobenzone 0.03 mL/1 mL

Glycolic Day Cream SPF 30

Active ingredients

Active ingredients Purpose

Homosalate 10.0% . . . . . Sunscreen

Octisalate 5.0% . . . . . . . Sunscreen

Oxybenzone 5.0% . . . . .Sunscreen

Avobenzone 3.0% . . . .Sunscreen

Octocrylene 2.0% . . . . Sunscreen

Keep out of reach of children. Do not swallow. If swallowed, get medical help or contact a Posion Control Center right away.